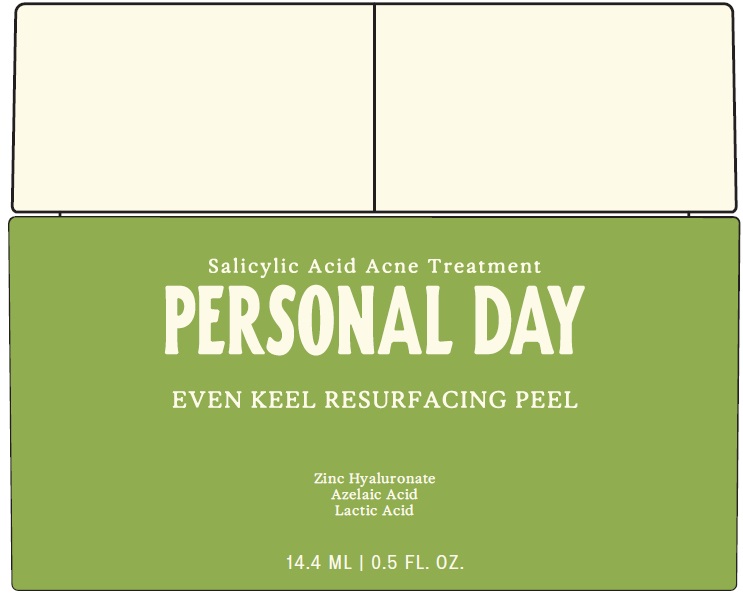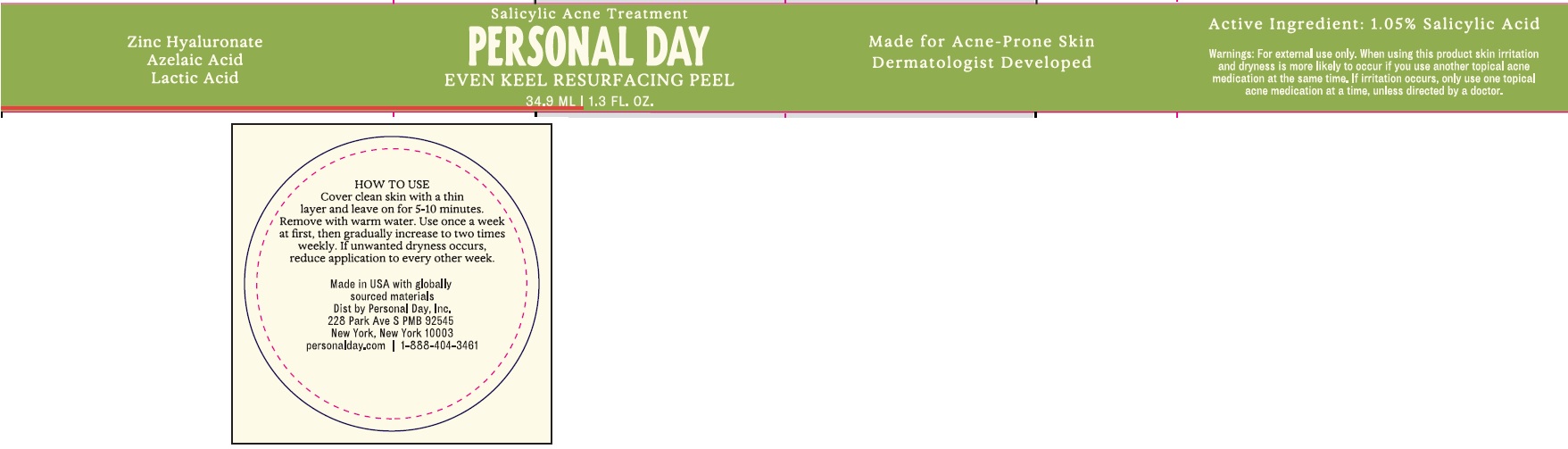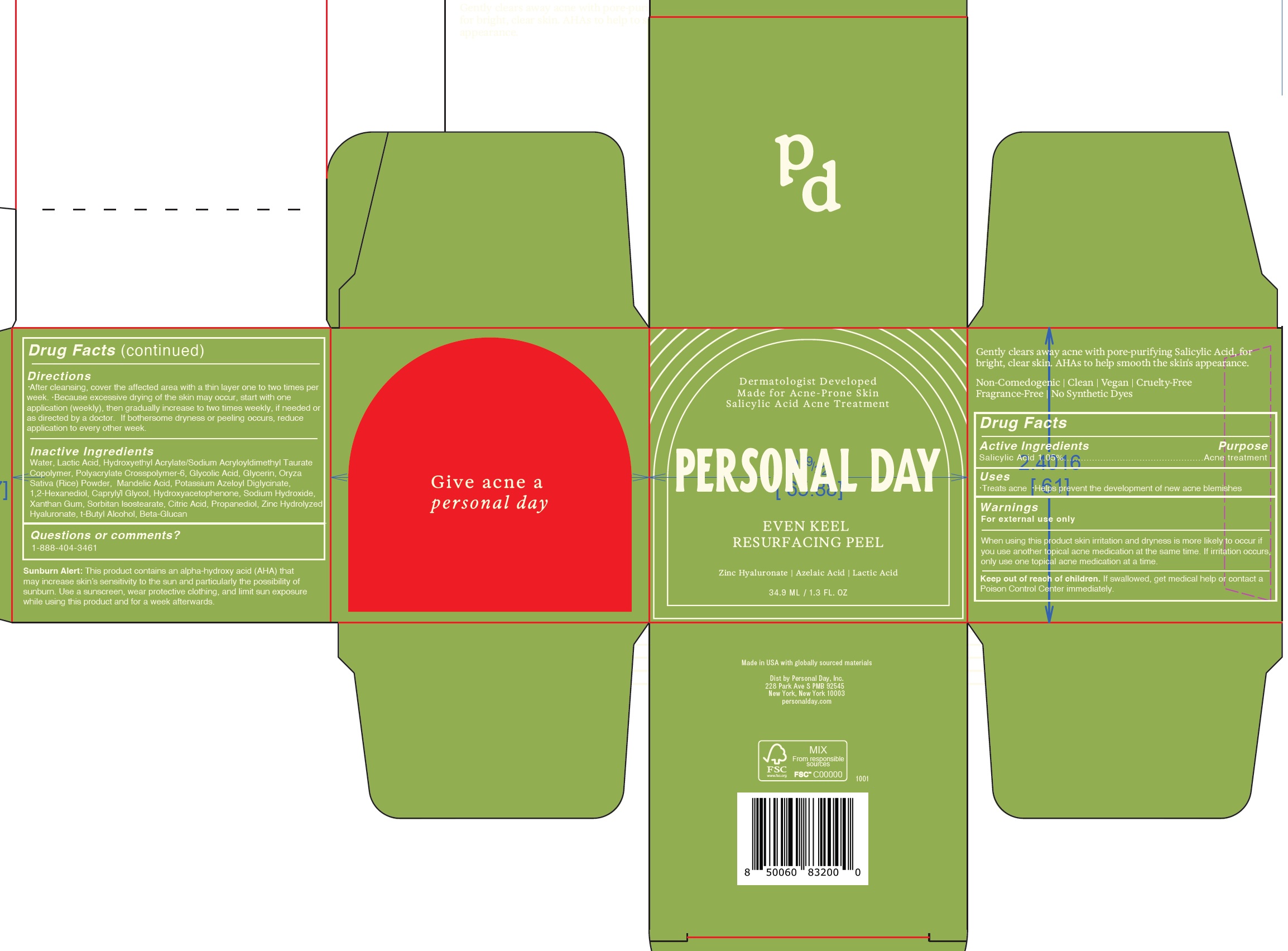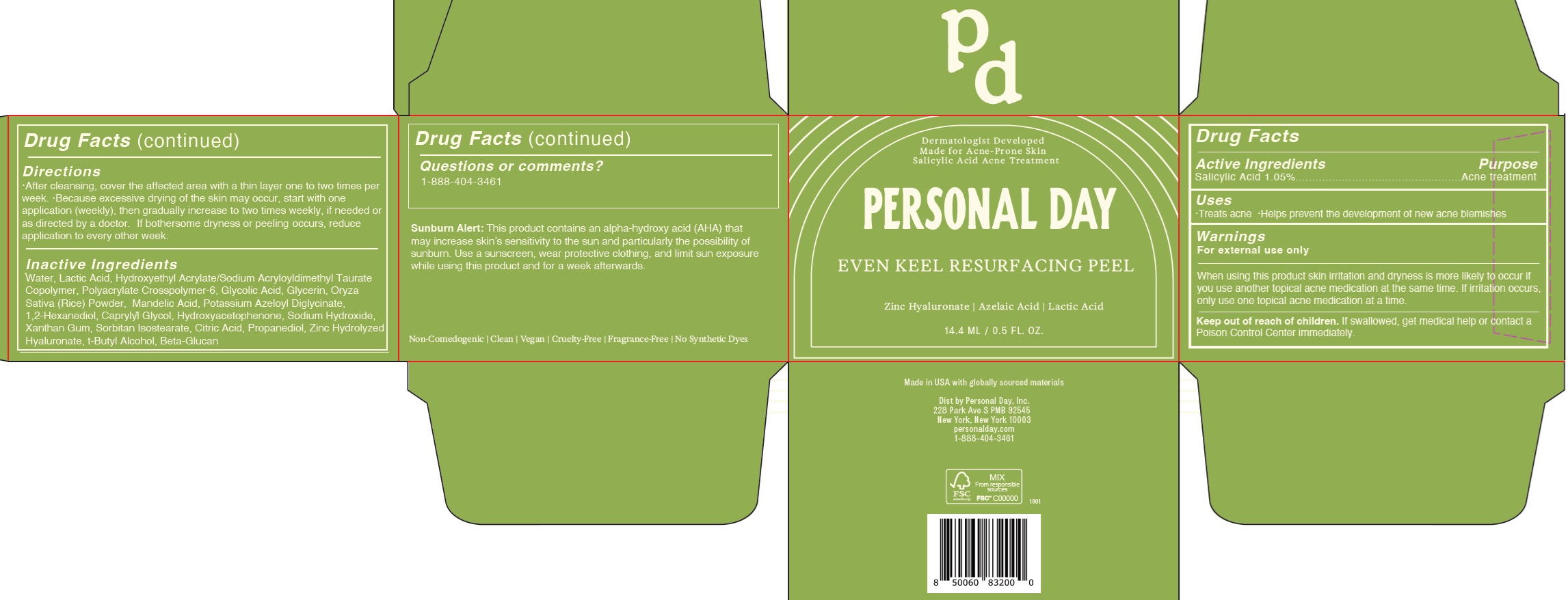 DRUG LABEL: EVEN KEEL RESURFACING PEEL
NDC: 84234-000 | Form: GEL
Manufacturer: Personal Day Inc.
Category: otc | Type: HUMAN OTC DRUG LABEL
Date: 20241210

ACTIVE INGREDIENTS: SALICYLIC ACID 10.5 mg/1 mL
INACTIVE INGREDIENTS: WATER; LACTIC ACID; AMMONIUM ACRYLOYLDIMETHYLTAURATE, DIMETHYLACRYLAMIDE, LAURYL METHACRYLATE AND LAURETH-4 METHACRYLATE COPOLYMER, TRIMETHYLOLPROPANE TRIACRYLATE CROSSLINKED (45000 MPA.S); GLYCOLIC ACID; GLYCERIN; WHITE RICE; MANDELIC ACID; POTASSIUM AZELOYL DIGLYCINATE; 1,2-HEXANEDIOL; CAPRYLYL GLYCOL; HYDROXYACETOPHENONE; SODIUM HYDROXIDE; XANTHAN GUM; SORBITAN ISOSTEARATE; CITRIC ACID MONOHYDRATE; PROPANEDIOL; TERT-BUTYL ALCOHOL

EVEN KEEL RESURFACING PEEL

Active Ingredients

Salicylic Acid 1.05%

Purpose

Acne treatment

Uses

- Treats acne
- Helps prevent the development of new acne blemishes

Warnings

For external use only

When using this product

skin irritation and dryness is more likely to occur if you use another topical acne medication at the same time. If irritation occurs, only use one topical acne medication at a time.

Keep out of reach of children.

If swallowed, get medical help or contact a Poison Control Center immediately.

Directions

- After cleansing, cover the affected area with a thin layer one to two times per week.
- Because excessive drying of the skin may occur, start with one application (weekly), then gradually increase to two times weekly, if needed or as directed by a doctor.
- If bothersome dryness or peeling occurs, reduce application to every other week.

Inactive Ingredients

Water, Lactic Acid, Hydroxyethyl Acrylate/Sodium Acryloyldimethyl Taurate Copolymer, Polyacrylate Crosspolymer-6, Glycolic Acid, Glycerin, Oryza Sativa (Rice) Powder, Mandelic Acid, Potassium Azeloyl Diglycinate, 1,2-Hexanediol, Caprylyl Glycol, Hydroxyacetophenone, Sodium Hydroxide, Xanthan Gum, Sorbitan Isostearate, Citric Acid, Propanediol, Zinc Hydrolyzed Hyaluronate, t-Butyl Alcohol, Beta-Glucan

Questions or comments?

1-888-404-3461